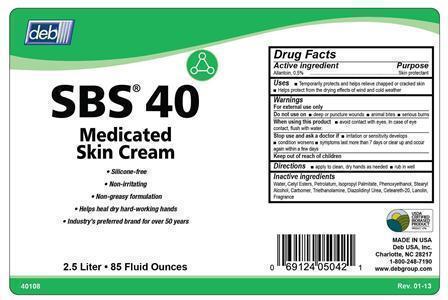 DRUG LABEL: SBS 40
NDC: 11084-240 | Form: CREAM
Manufacturer: Deb USA, Inc.
Category: otc | Type: HUMAN OTC DRUG LABEL
Date: 20170215

ACTIVE INGREDIENTS: ALLANTOIN 5 mg/100 mL
INACTIVE INGREDIENTS: WATER; CARBOMER 934; CETYL ESTERS WAX; PETROLATUM; ISOPROPYL PALMITATE; LANOLIN; TRIETHANOLAMINE BENZOATE; DIAZOLIDINYL UREA; PHENOXYETHANOL; POLYOXYL 20 CETOSTEARYL ETHER

SBS 40

Active ingredient

Allantoin, 0.5%

Purpose

Skin Protectant

Uses

Temporarily protects and helps relieve chapped or cracked skin

Helps protect from the drying effects of wind and cold weather

Warnings

For external use only

Do not use on

deep or puncture wounds

animal bites

serious burns

When using this product

avoid contact with eyes.

In case of eye contact, flush with water.

Stop use and ask a doctor if

irritation or sensitivity develops

condition worsens

symptoms last more than 7 days or clear up and occur again within a few days

Keep out of reach of children

Directions

apply to clean, dry hands as needed

rub in well

Inactive ingredients

Water, Cetyl Esters, Petrolatum, Isopropyl Palmitate, Phenoxyethanol, Stearyl Alcohol, Carbomer, Triethanolamine, Diazolidinyl Urea, Ceteareth-20, Lanolin, Fragrance

PACKAGE LABEL

deb

SBS 40

Medicated Skin Cream

Silicone-free

Non-irritating

Non-greasy formulation

Helps heal dry hard-working hands

Industry's preferred brand for over 50 years

2.5 Liter

85 Fluid Ounces

USDA Certified Biobased Product

Made in USA

Deb USA, Inc.

Charlotte, NC 28217

1-800-248-7190

www.debgroup.com

40108

Rev. 01-13